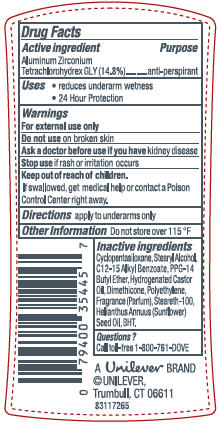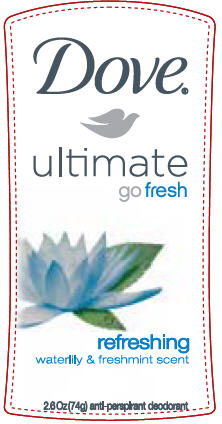 DRUG LABEL: Dove Ultimate Go Fresh Refreshing
NDC: 64942-1052 | Form: STICK
Manufacturer: Conopco Inc. d/b/a Unilever
Category: otc | Type: HUMAN OTC DRUG LABEL
Date: 20100608

ACTIVE INGREDIENTS: Aluminum Zirconium Tetrachlorohydrex GLY 14.8 g/100 g

Dove Ultimate Go Fresh Refreshing Antiperspirant and Deodorant PDP and drug facts

Active ingredient Purpose

Aluminum Zirconium Tetrachlorohydrex GLY(14.8%)............anti-perspirant

Warning
For external use only

Do not use on broken skin

Ask a doctor before use if you have kidney disease

Stop use if rash or irritation occurs

Keep out of reach of children. If swallowed, get medical help or contact a Poison Control Center right away.

Inactive ingredients

Cyclopentasiloxane, Stearyl Alcohol, C12-15 Alkyl Benzoate, PPG-14 Butyl Ether, Hydrogenated Castor Oil, Dimethicone, Polyethylene, Fragrance (Parfum), Steareth-100, Helianthus Annuus (Sunflower) Seed Oil, BHT.

Questions?

Call toll-free 1-800-761-DOVE

PACKAGE LABEL

PDP 2.6 oz front

PACKAGE LABEL

PDP 2.6 oz back